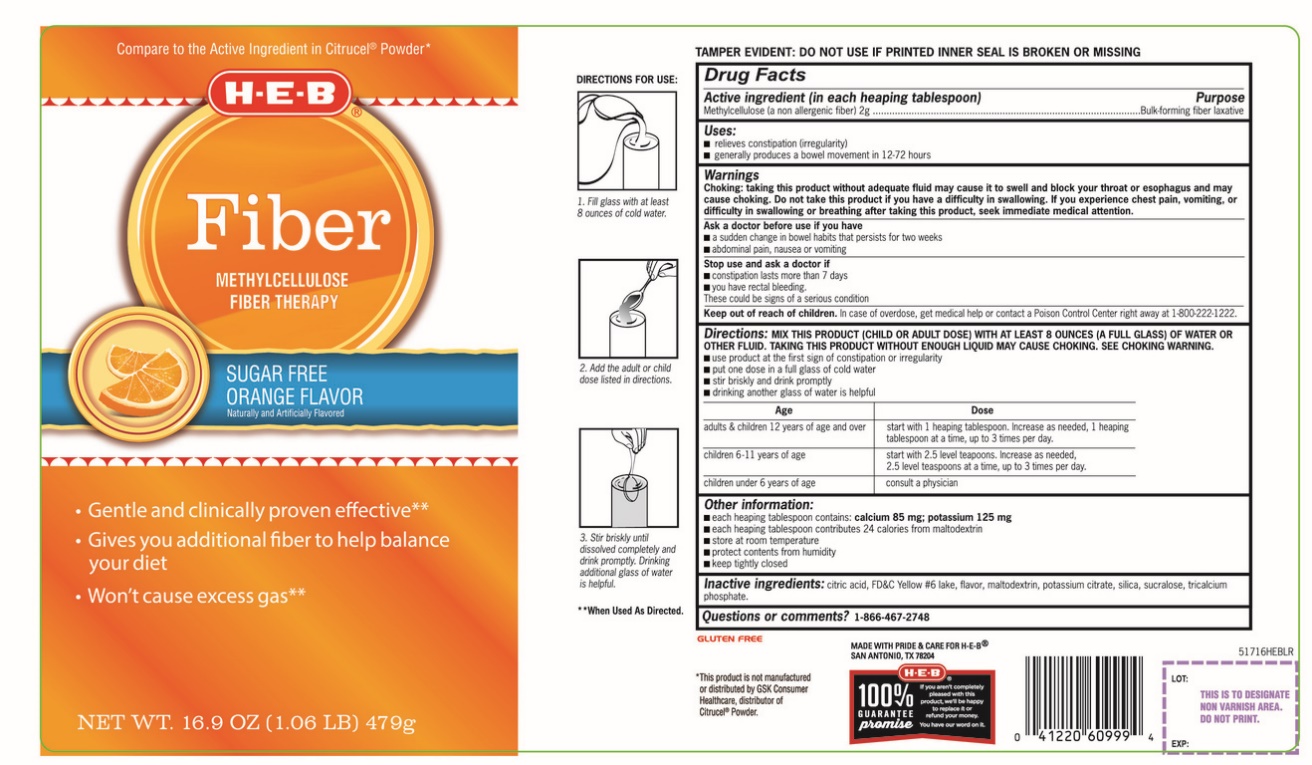 DRUG LABEL: HEB Fiber Therapy
NDC: 37808-716 | Form: POWDER, FOR SOLUTION
Manufacturer: HEB
Category: otc | Type: HUMAN OTC DRUG LABEL
Date: 20251003

ACTIVE INGREDIENTS: METHYLCELLULOSE (4000 MPA.S) 2 g/10.2 g
INACTIVE INGREDIENTS: ANHYDROUS CITRIC ACID; FD&C YELLOW NO. 6; MALTODEXTRIN; POTASSIUM CITRATE; SILICON DIOXIDE; SUCRALOSE; TRICALCIUM PHOSPHATE

HEB Fiber Therapy Methylcellulose 2 g Bulk Forming Laxative

Active ingredient(in each rounded tablespoon)

(in each rounded tablespoon)

Methylcellulose (a non-allergenic fiber) 2g

Purpose

Bulk-forming fiber laxative

Uses

- relieves constipation (irregularity)
- generally produces a bowel movement in 12-72 hours

Warnings

Choking: taking this product without adequate fluid may cause it to swell and block your throat or esophagus and may cause choking. Do not take this product if you have difficulty in swallowing. If you experience chest pain, vomiting, or difficulty in swallowing or breathing after taking this product, seek immediate medical attention.

Ask a doctor before use if you have

- a sudden change in bowel habits that persists for two weeks
- abdominal pain, nausea or vomiting

Stop use and ask a doctor if

- constipation lasts more than 7 days
- you have rectal bleeding

These could be signs of a serious condition.

Keep out of reach of children.

In case of overdose, get medical help or contact a Poison Control Center right away at 1-800-222-1222.

Directions

- MIX THIS PRODUCT (CHILD OR ADULT DOSE) WITH AT LEAST 8 OUNCES (A FULL GLASS) OF WATER OR OTHER FLUID. TAKING THIS PRODUCT WITHOUT ENOUGH LIQUID MAY CAUSE CHOKING. SEE CHOKING WARNING
- use product at the first sign of constipation or irregularity
- put one dose in a full glass of cold water
- stir briskly and drink promptly
- drinking another glass of water is helpful

Age | Dose
adults & children 12 years of age and over | start with 1 heaping tablespoon. Increase as needed, 1 heaping tablespoonat a time, up to 3 times per day.
children 6 - 11 years of age | start with 2.5 level teaspoons. Increase as needed, 2.5 level teaspoonsat a time, up to 3 times per day.
children under 6 years of age | consult a physician

Other information

- each heaping tablespoon contains: calcium 85mg and potassium 125mg
- each heaping tablespoon contributes 24 calories from maltodextrin
- store below at room temperature
- protect contents from humidity
- keep tightly closed

Inactive ingredients

citric acid, FD&C yellow #6 lake, flavor, maltodextrin, potassium citrate, silica, sucralose, tricalcium phosphate,

Questions or comments?

1-866-467-2748

Principal Display Panel

HEB®

Compare to the Active Ingredient in Citrucel®Powder*

NDC 37808-716-16

Fiber

METHYLCELLULOSE FIBER THERAPY

- Gentle and clinically proven effective**
- Gives you additional fiber to help balance your diet
- Won’t cause excess gas**

SUGAR FREE

ORANGE FLAVOR

Naturally & Artificially Flavored

NET WT 16.9 OZ (1.06 LB) (479g)

Directions for use:

1. Fill glass with at least 8 ounces of cold water.
2. Add the recommended dose listed in directions.
3. Stir briskly until dissolved completely and drink promptly .Drinking an additional glass of water is helpful.

TAMPER EVIDENT: DO NOT USE PRINTED INNER SEAL IS BROKEN OR MISSING

GLUTEN FREE

*This product is not manufactured or distributed by GlaxoSmithKline, the distributor of Citrucel®.

MADE WITH PRIDE & CARE FOR H-E-B

SAN ANTONIO, TX 78204

100% GUARANTEE promise

If you aren’t completely pleased with this product, we’ll be happy to replace it or refund your money. You have our word on it.